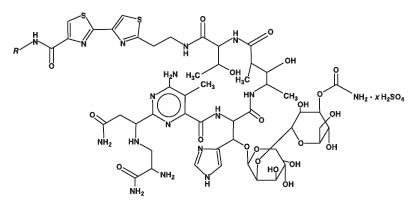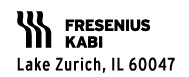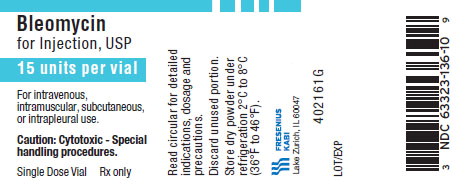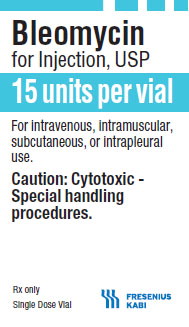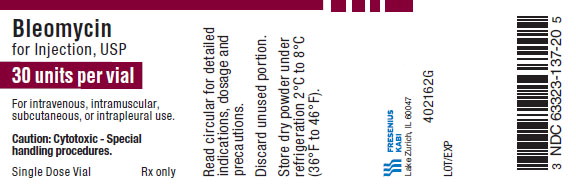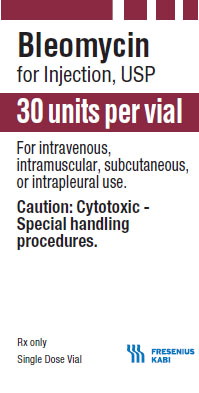 DRUG LABEL: Bleomycin

NDC: 63323-137 | Form: INJECTION, POWDER, LYOPHILIZED, FOR SOLUTION
Manufacturer: Fresenius Kabi USA, LLC
Category: prescription | Type: HUMAN PRESCRIPTION DRUG LABEL
Date: 20241010

ACTIVE INGREDIENTS: BLEOMYCIN SULFATE 30 [USP'U]/1 1

Bleomycin for Injection, USP

Rx only

BOXED WARNING

It is recommended that Bleomycin for Injection, USP be administered under the supervision of a qualified physician experienced in the use of cancer chemotherapeutic agents. Appropriate management of therapy and complications is possible only when adequate diagnostic and treatment facilities are readily available.

Pulmonary fibrosis is the most severe toxicity associated with bleomycin. The most frequent presentation is pneumonitis occasionally progressing to pulmonary fibrosis. Its occurrence is higher in elderly patients and in those receiving greater than 400 units total dose, but pulmonary toxicity has been observed in young patients and those treated with low doses.

A severe idiosyncratic reaction consisting of hypotension, mental confusion, fever, chills, and wheezing has been reported in approximately 1% of lymphoma patients treated with bleomycin.

DESCRIPTION:

Bleomycin for Injection, USP is a mixture of cytotoxic glycopeptide antibiotics isolated from a strain of Streptomyces verticillus. It is freely soluble in water.

Bleomycin for Injection, USP is provided as a sterile lyophilized powder for reconstitution containing 15 units per vial and 30 units per vial, which are intended for intramuscular, intravenous, subcutaneous or intrapleural administration.

Its chemical name is N’-[3-(dimethylsulphonio)propyl]bleomycin-amide (bleomycin A2) and N’-[4-(guaniodobutyl)]bleomycin-amide (bleomycin B2).

(Main component: Bleomycin A2, in which R is [CH3]2S^+CH2CH2CH2-)

Note: A unit of bleomycin is equal to the formerly used milligram activity. The term milligram activity is a misnomer and was changed to units to be more precise.

CLINICAL PHARMACOLOGY:

Mechanism of Action

Although the exact mechanism of action of bleomycin is unknown, available evidence indicates that the main mode of action is the inhibition of DNA synthesis with some evidence of lesser inhibition of RNA and protein synthesis.

Bleomycin is known to cause single, and to a lesser extent, double-stranded breaks in DNA. In in vitro and in vivo experiments, bleomycin has been shown to cause cell cycle arrest in G2 and in mitosis.

When administered into the pleural cavity in the treatment of malignant pleural effusion, bleomycin acts as a sclerosing agent.

Pharmacokinetics

Absorption

Bleomycin is rapidly absorbed following either intramuscular, subcutaneous, intraperitoneal, or intrapleural administration reaching peak plasma concentrations in 30 to 60 minutes. Systemic bioavailability of bleomycin is 100% and 70% following intramuscular and subcutaneous administrations, respectively, and 45% following both intraperitoneal and intrapleural administrations, compared to intravenous and bolus administration.

Following intramuscular doses of 1 to 10 units/m^2, both peak plasma concentration and AUC increased in proportion with the increase of dose.

Following intravenous bolus administration of 30 units of bleomycin to one patient with a primary germ cell tumor of the brain, a peak CSF level was 40% of the simultaneously-obtained plasma level and was attained in 2 hours after drug administration. The area under the bleomycin CSF concentration x time curve was 25% of the area of the bleomycin plasma concentration x time curve.

Distribution

Bleomycin is widely distributed throughout the body with a mean volume of distribution of 17.5 L/m^2 in patients following a 15 units/m^2 intravenous bolus dose. Protein binding of bleomycin has not been studied.

Metabolism

Bleomycin is inactivated by a cytosolic cysteine proteinase enzyme, bleomycin hydrolase. The enzyme is widely distributed in normal tissues with the exception of the skin and lungs, both targets of bleomycin toxicity. Systemic elimination of the drug by enzymatic degradation is probably only important in patients with severely compromised renal function.

Excretion

The primary route of elimination is via the kidneys. About 65% of the administered intravenous dose is excreted in urine within 24 hours. In patients with normal renal function, plasma concentrations of bleomycin decline biexponentially with a mean terminal half-life of 2 hours following intravenous bolus administration. Total body clearance and renal clearance averaged 51 mL/min/m^2 and 23 mL/min/m^2, respectively.

Following intrapleural administration to patients with normal renal function, a lower percentage of drug (40%) is recovered in the urine, as compared to that found in the urine after intravenous administration.

Special Populations

Age, Gender, and Race

The effects of age, gender, and race on the pharmacokinetics of bleomycin have not been evaluated.

Pediatric

Children of less than 3 years of age have higher total body clearance than in adults, 71 mL/min/m^2 versus 51 mL/min/m^2, respectively, following intravenous bolus administration. Children of more than 8 years of age have comparable clearance as in adults.

In children with normal renal function, plasma concentrations of bleomycin decline biexponentially as in adults. The volume of distribution and terminal half-life of bleomycin in children appears comparable to that in adults.

Renal Insufficiency

Renal insufficiency markedly alters bleomycin elimination. The terminal elimination half-life increases exponentially as the creatinine clearance decreases. Dosing reductions were proposed for patients with creatinine clearance values of <50 mL/min (see PRECAUTIONS and DOSAGE AND ADMINISTRATION).

Hepatic Insufficiency

The effect of hepatic insufficiency on the pharmacokinetics of bleomycin has not been evaluated.

Drug Interactions

Drugs that Can Affect Renal Clearance

Because bleomycin is eliminated predominantly through renal excretion, the administration of nephrotoxic drugs with bleomycin may affect its renal clearance. Specifically, in one report of 2 children receiving concomitant cisplatin with bleomycin, total body clearance of bleomycin decreased from 39 to 18 mL/min/m^2 as the cumulative dose of cisplatin exceeded 300 mg/m^2. Terminal half-life of bleomycin also increased from 4.4 to 6 hours. Fatal bleomycin pulmonary toxicity has been reported in a patient with unrecognized cisplatin-induced oliguric renal failure.

Clinical Studies

Malignant Pleural Effusion

The safety and efficacy of bleomycin 60 units and tetracycline (1 g) as treatment for malignant pleural effusion were evaluated in a multicenter, randomized trial. Patients were required to have cytologically positive pleural effusion, good performance status (0,1,2), lung re-expansion following tube thoracostomy with drainage rates of 100 mL/24 hours or less, no prior intrapleural therapy, no prior systemic bleomycin therapy, no chest irradiation, and no recent change in systemic therapy. Overall survival did not differ between the bleomycin (n=44) and tetracycline treatment (n=41) groups. Of patients evaluated within 30 days of instillation, the recurrence rate was 36% (10/28) with bleomycin and 67% (18/27) with tetracycline (p=0.023). Toxicity was similar between groups.

INDICATIONS AND USAGE:

Bleomycin for Injection, USP should be considered a palliative treatment. It has been shown to be useful in the management of the following neoplasms either as a single agent or in proven combinations with other approved chemotherapeutic agents:

Squamous Cell Carcinoma: Head and neck (including mouth, tongue, tonsil, nasopharynx, oropharynx, sinus, palate, lip, buccal mucosa, gingivae, epiglottis, skin, larynx), penis, cervix, and vulva. The response to Bleomycin for Injection is poorer in patients with previously irradiated head and neck cancer.

Lymphomas: Hodgkin’s disease, non-Hodgkin’s lymphoma.

Testicular Carcinoma: Embryonal cell, choriocarcinoma, and teratocarcinoma.

Bleomycin for Injection, USP has also been shown to be useful in the management of:

Malignant Pleural Effusion: Bleomycin for Injection is effective as a sclerosing agent for the treatment of malignant pleural effusion and prevention of recurrent pleural effusions.

CONTRAINDICATIONS:

Bleomycin for Injection is contraindicated in patients who have demonstrated a hypersensitive or an idiosyncratic reaction to it.

WARNINGS:

Patients receiving bleomycin must be observed carefully and frequently during and after therapy. It should be used with extreme caution in patients with significant impairment of renal function or compromised pulmonary function.

Pulmonary toxicities occur in 10% of treated patients. In approximately 1%, the nonspecific pneumonitis induced by bleomycin progresses to pulmonary fibrosis and death. Although this is age and dose related, the toxicity is unpredictable. Frequent roentgenograms are recommended (see ADVERSE REACTIONS, Pulmonary).

A severe idiosyncratic reaction (similar to anaphylaxis) consisting of hypotension, mental confusion, fever, chills, and wheezing has been reported in approximately 1% of lymphoma patients treated with bleomycin. Since these reactions usually occur after the first or second dose, careful monitoring is essential after these doses (see ADVERSE REACTIONS, Idiosyncratic Reactions).

Renal or hepatic toxicity, beginning as a deterioration in renal or liver function tests, have been reported. These toxicities may occur at any time after initiation of therapy.

Usage in Pregnancy

Pregnancy “Category D”

Bleomycin can cause fetal harm when administered to a pregnant woman. It has been shown to be teratogenic in rats. Administration of intraperitoneal doses of 1.5 mg/kg/day to rats (about 1.6 times the recommended human dose on a unit/m^2 basis) on days 6 to 15 of gestation caused skeletal malformations, shortened innominate artery and hydroureter. Bleomycin is abortifacient but not teratogenic in rabbits at intravenous doses of 1.2 mg/kg/day (about 2.4 times the recommended human dose on a unit/m^2 basis) given on gestation days 6 to 18.

There have been no studies in pregnant women. If bleomycin is used during pregnancy, or if the patient becomes pregnant while receiving this drug, the patient should be apprised of the potential hazard to the fetus. Women of childbearing potential should be advised to avoid becoming pregnant during therapy with bleomycin.

PRECAUTIONS:

General

Patients with creatinine clearance values of less than 50 mL/min should be treated with caution and their renal function should be carefully monitored during the administration of bleomycin. Lower doses of bleomycin may be required in these patients than those with normal renal function (see CLINICAL PHARMACOLOGY and DOSAGE AND ADMINISTRATION).

Carcinogenesis, Mutagenesis, Impairment of Fertility

The carcinogenic potential of bleomycin in humans is unknown. A study in F344-type male rats demonstrated an increased incidence of nodular hyperplasia after induced lung carcinogenesis by nitrosamines, followed by treatment with bleomycin. In another study where the drug was administered to rats by subcutaneous injection at 0.35 mg/kg weekly (3.82 units/m^2 weekly or about 30% at the recommended human dose), necropsy findings included dose-related injection site fibrosarcomas as well as various renal tumors. Bleomycin has been shown to be mutagenic both in vitro and in vivo. The effects of bleomycin on fertility have not been studied.

Pregnancy

Pregnancy “Category D”

(See WARNINGS.)

Nursing Mothers

It is not known whether the drug is excreted in human milk. Because many drugs are excreted in human milk and because of the potential for serious adverse reactions in nursing infants, it is recommended that nursing be discontinued by women receiving bleomycin therapy.

Pediatric Use

Safety and effectiveness of bleomycin in pediatric patients have not been established.

Geriatric Use

In clinical trials, pulmonary toxicity was more common in patients older than 70 years than in younger patients (see BOXED WARNING, WARNINGS, and ADVERSE REACTIONS, Pulmonary). Other reported clinical experience has not identified other differences in responses between elderly and younger patients, but greater sensitivity of some older individuals cannot be ruled out.

Bleomycin is known to be substantially excreted by the kidney, and the risk of toxic reactions to this drug may be greater in patients with impaired renal function. Because elderly patients are more likely to have decreased renal function, care should be taken in dose selection, and it may be useful to monitor renal function.

ADVERSE REACTIONS:

Pulmonary

The most serious side effects are pulmonary adverse reactions, occurring in approximately 10% of treated patients. The most frequent presentation is pneumonitis occasionally progressing to pulmonary fibrosis. Approximately 1% of patients treated have died of pulmonary fibrosis. Pulmonary toxicity is both dose and age related, being more common in patients over 70 years of age and in those receiving over 400 units total dose. This toxicity, however, is unpredictable and has been seen in young patients receiving low doses. Some published reports have suggested that the risk of pulmonary toxicity may be increased when bleomycin is used in combination with G-CSF (filgrastim) or other cytokines. However, randomized clinical studies completed to date have not demonstrated an increased risk of pulmonary complications in patients treated with bleomycin and G-CSF.

Because of lack of specificity of the clinical syndrome, the identification of patients with pulmonary toxicity due to bleomycin has been extremely difficult. The earliest symptom associated with bleomycin pulmonary toxicity is dyspnea. The earliest sign is fine rales.

Radiographically, bleomycin-induced pneumonitis produces nonspecific patchy opacities, usually of the lower lung fields. The most common changes in pulmonary function tests are a decrease in total lung volume and a decrease in vital capacity. However, these changes are not predictive of the development of pulmonary fibrosis.

The microscopic tissue changes due to bleomycin toxicity include bronchiolar squamous metaplasia, reactive macrophages, atypical alveolar epithelial cells, fibrinous edema, and interstitial fibrosis. The acute stage may involve capillary changes and subsequent fibrinous exudation into alveoli producing a change similar to hyaline membrane formation and progressing to a diffuse interstitial fibrosis resembling the Hamman-Rich syndrome. These microscopic findings are nonspecific; e.g., similar changes are seen in radiation pneumonitis and pneumocystic pneumonitis.

To monitor the onset of pulmonary toxicity, roentgenograms of the chest should be taken every 1 to 2 weeks (see WARNINGS). If pulmonary changes are noted, treatment should be discontinued until it can be determined if they are drug related. Recent studies have suggested that sequential measurement of the pulmonary diffusion capacity for carbon monoxide (DLco) during treatment with bleomycin may be an indicator of subclinical pulmonary toxicity. It is recommended that the DLco be monitored monthly if it is to be employed to detect pulmonary toxicities, and thus the drug should be discontinued when the DLco falls below 30% to 35% of the pretreatment value.

Because of bleomycin’s sensitization of lung tissue, patients who have received bleomycin are at greater risk of developing pulmonary toxicity when oxygen is administered in surgery. While long exposure to very high oxygen concentrations is a known cause of lung damage, after bleomycin administration, lung damage can occur at lower concentrations that are usually considered safe. Suggested preventive measures are:

1. Maintain FlO2 at concentrations approximating that of room air (25%) during surgery and the postoperative period.

2. Monitor carefully fluid replacement, focusing more on colloid administration rather than crystalloid.

Sudden onset of an acute chest pain syndrome suggestive of pleuropericarditis has been reported during bleomycin infusions. Although each patient must be individually evaluated, further courses of bleomycin do not appear to be contraindicated.

Pulmonary adverse events which may be related to the intrapleural administration of bleomycin have been reported.

Idiosyncratic Reactions

In approximately 1% of the lymphoma patients treated with bleomycin, an idiosyncratic reaction, similar to anaphylaxis clinically, has been reported. The reaction may be immediate or delayed for several hours, and usually occurs after the first or second dose (see WARNINGS). It consists of hypotension, mental confusion, fever, chills, and wheezing. Treatment is symptomatic including volume expansion, pressor agents, antihistamines, and corticosteroids.

Integument and Mucous Membranes

These adverse reactions have been reported in approximately 50% of treated patients. They consist of erythema, rash, striae, vesiculation, hyperpigmentation, and tenderness of the skin. Hyperkeratosis, nail changes, alopecia, pruritus, and stomatitis have also been reported. It was necessary to discontinue bleomycin therapy in 2% of treated patients because of these toxicities.

Scleroderma-like skin changes have been reported.

Skin toxicity is a relatively late manifestation usually developing in the second and third week of treatment after 150 to 200 units of bleomycin have been administered and appears to be related to the cumulative dose.

Intrapleural administration of bleomycin has been associated with local pain. Hypotension possibly requiring symptomatic treatment has been reported. Death has been reported in association with bleomycin pleurodesis in seriously ill patients.

Other

Vascular toxicities coincident with the use of bleomycin in combination with other antineoplastic agents have been reported. The events are clinically heterogeneous and may include myocardial infarction, cerebrovascular accident, thrombotic microangiopathy (HUS), or cerebral arteritis. Various mechanisms have been proposed for these vascular complications. There are also reports of Raynaud’s phenomenon occurring in patients treated with bleomycin in combination with vinblastine with or without cisplatin or, in a few cases, with bleomycin as a single agent. It is currently unknown if the cause of Raynaud’s phenomenon in these cases is the disease, underlying vascular compromise, bleomycin, vinblastine, hypomagnesemia, or a combination of any of these factors.

Fever, chills, and vomiting have been reported. Anorexia and weight loss have been reported and may persist long after termination of this medication. Pain at tumor site, phlebitis, and other local reactions have been reported.

Malaise has been reported.

DOSAGE AND ADMINISTRATION:

Because of the possibility of an anaphylactoid reaction, lymphoma patients should be treated with 2 units or less for the first 2 doses. If no acute reaction occurs, then the regular dosage schedule may be followed.

The following dose schedule is recommended:

Squamous cell carcinoma, non-Hodgkin’s lymphoma, testicular carcinoma– 0.25 to 0.5 units/kg (10 to 20 units/m^2) given intravenously, intramuscularly, or subcutaneously weekly or twice weekly.

Hodgkin’s Disease – 0.25 to 0.5 units/kg (10 to 20 units/m^2) given intravenously, intramuscularly, or subcutaneously weekly or twice weekly. After a 50% response, a maintenance dose of 1 unit daily or 5 units weekly intravenously or intramuscularly should be given.

Pulmonary toxicity of Bleomycin for Injection, USP appears to be dose-related with a striking increase when the total dose is over 400 units. Total doses over 400 units should be given with great caution.

Note: When Bleomycin for Injection, USP is used in combination with other antineoplastic agents, pulmonary toxicities may occur at lower doses.

Improvement of Hodgkin’s disease and testicular tumors is prompt and noted within 2 weeks. If no improvement is seen by this time, improvement is unlikely. Squamous cell cancers respond more slowly, sometimes requiring as long as 3 weeks before any improvement is noted.

Malignant Pleural Effusion – 60 units administered as a single dose bolus intrapleural injection (see ADMINISTRATION, Intrapleural).

Use in Patients with Renal Insufficiency

The following dosing reductions are proposed for patients with creatinine clearance (CrCL) values of less than 50 mL/min:

Patient CrCL (mL/min) | Bleomycin for Injection, USP Dose (%)
50 and above | 100
40 to 50 | 70
30 to 40 | 60
20 to 30 | 55
10 to 20 | 45
5 to 10 | 40

CrCL can be estimated from the individual patient’s measured serum creatinine (Scr) values using the Cockcroft and Gault formula:

Males CrCL = [weight x (140 – Age)]/(72 x Scr)

Females CrCL = 0.85 x [weight x (140 – Age)]/(72 x Scr)

Where CrCL in mL/min/1.73 m^2, weight in kg, age in years, and Scr in mg/dL.

ADMINISTRATION:

Bleomycin for Injection may be given by the intramuscular, intravenous, subcutaneous, or intrapleural routes.

Administration Precautions

Caution should be exercised when handling Bleomycin for Injection. Procedures for proper handling and disposal of anticancer drugs should be utilized. Several guidelines on this subject have been published.^1-4 To minimize the risk of dermal exposure, always wear impervious gloves when handling vials containing Bleomycin for Injection. If Bleomycin for Injection contacts the skin, immediately wash the skin thoroughly with soap and water. If contact with mucous membranes occurs, the membranes should be flushed immediately and thoroughly with water. More information is available in the references listed below.

Intramuscular or Subcutaneous

The Bleomycin for Injection 15 units vial should be reconstituted with 1 to 5 mL of Sterile Water for Injection, USP, Sodium Chloride for Injection, 0.9%, USP, or Sterile Bacteriostatic Water for Injection, USP. The Bleomycin for Injection 30 units vial should be reconstituted with 2 to 10 mL of the above diluents.

Intravenous

The contents of the 15 units or 30 units vial should be dissolved in 5 mL or 10 mL, respectively, of Sodium Chloride for Injection, 0.9%, USP, and administered slowly over a period of 10 minutes.

Intrapleural

Sixty units of Bleomycin for Injection are dissolved in 50 to 100 mL Sodium Chloride for Injection, 0.9%, USP, and administered through a thoracostomy tube following drainage of excess pleural fluid and confirmation of complete lung expansion. The literature suggests that successful pleurodesis is, in part, dependent upon complete drainage of the pleural fluid and re-establishment of negative intrapleural pressure prior to instillation of a sclerosing agent. Therefore, the amount of drainage from the chest tube should be as minimal as possible prior to instillation of Bleomycin for Injection. Although there is no conclusive evidence to support this contention, it is generally accepted that chest tube drainage should be less than 100 mL in a 24-hour period prior to sclerosis. However, Bleomycin for Injection instillation may be appropriate when drainage is between 100 to 300 mL under clinical conditions that necessitate sclerosis therapy. The thoracostomy tube is clamped after Bleomycin for Injection instillation. The patient is moved from the supine to the left and right lateral positions several times during the next four hours. The clamp is then removed and suction re-established. The amount of time the chest tube remains in place following sclerosis is dictated by the clinical situation.

The intrapleural injection of topical anesthetics or systemic narcotic analgesia is generally not required.

Parenteral drug products should be inspected visually for particulate matter and discoloration prior to administration, whenever solution and container permit.

HOW SUPPLIED:

Bleomycin for Injection, USP is available as follows:

Product No. | NDC No.
103610 | 63323-136-10 | 15 units per vial, individually packaged.
103720 | 63323-137-20 | 30 units per vial, individually packaged.

Stability

The sterile powder is stable under refrigeration 2°C to 8°C (36°F to 46°F) and should not be used after the expiration date is reached.

Bleomycin for Injection should not be reconstituted or diluted with D5W or other dextrose containing diluents. When reconstituted in D5W and analyzed by HPLC, Bleomycin for Injection demonstrates a loss of A2 and B2 potency that does not occur when Bleomycin for Injection is reconstituted in Sodium Chloride for Injection, 0.9%, USP.

Bleomycin for Injection is stable for 24 hours at room temperature in Sodium Chloride.

The container closure is not made with natural rubber latex.

REFERENCES:

1. NIOSH Alert: Preventing occupational exposures to antineoplastic and other hazardous drugs in healthcare settings. 2004. U.S. Department of Health and Human Services, Public Health Service, Centers for Disease Control and Prevention, National Institute for Occupational Safety and Health, DHHS (NIOSH) Publication No. 2004-165.
2. OSHA Technical Manual, TED 1-0.15A, Section VI: Chapter 2. Controlling occupational exposure to hazardous drugs. OSHA, 1999. http://www.osha.gov/dts/osta/otm/otm_vi/otm_vi_2.html
3. American Society of Health-System Pharmacists. ASHP guidelines on handling hazardous drugs. Am J Health-Syst Pharm. 2006;63:1172-1193.
4. Polovich M, White JM, Kelleher LO, eds. 2005. Chemotherapy and biotherapy guidelines and recommendations for practice. 2nd ed. Pittsburgh, PA: Oncology Nursing Society.

www.fresenius-kabi.us
45998F

Revised: November 2016

PACKAGE LABEL

PACKAGE LABEL - PRINCIPAL DISPLAY - Bleomycin 15 units per vial Vial Label

Bleomycin for Injection, USP

15 units per vial

For intravenous, intramuscular, subcutaneous, or intrapleural use.

Caution: Cytotoxic - Special handling procedures.

Single Dose Vial

Rx only

PACKAGE LABEL - PRINCIPAL DISPLAY - Bleomycin 15 units per vial Carton Panel

Bleomycin for Injection, USP

15 units per vial

For intravenous, intramuscular, subcutaneous, or intrapleural use.

Caution: Cytotoxic - Special handling procedures.

Rx only
Single Dose Vial

PACKAGE LABEL - PRINCIPAL DISPLAY - Bleomycin 30 units per vial Vial Label

Bleomycin for Injection, USP

30 units per vial

For intravenous, intramuscular, subcutaneous, or intrapleural use.

Caution: Cytotoxic - Special handling procedures.

Single Dose Vial

Rx only

PACKAGE LABEL - PRINCIPAL DISPLAY - Bleomycin 30 units per vial Carton Panel

Bleomycin for Injection, USP

30 units per vial

For intravenous, intramuscular, subcutaneous, or intrapleural use.

Caution: Cytotoxic - Special handling procedures.

Rx only
Single Dose Vial